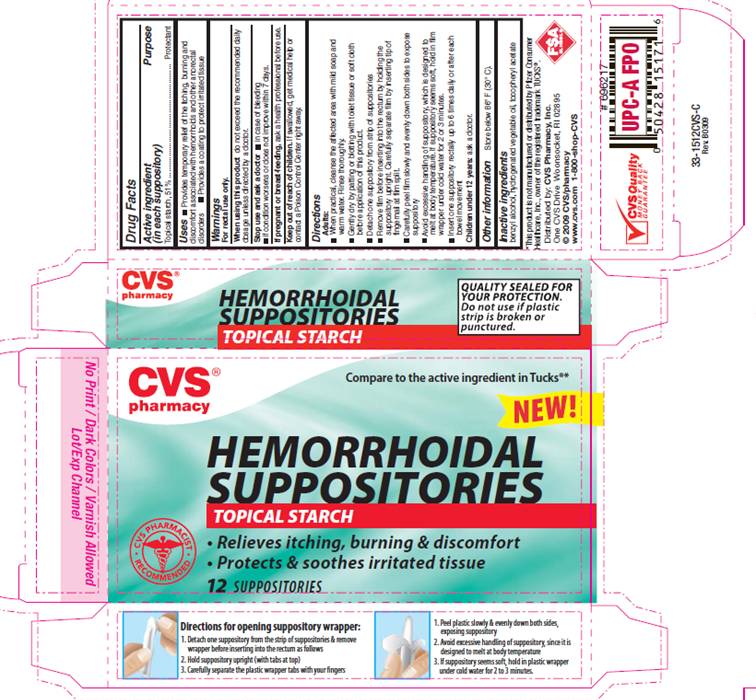 DRUG LABEL: Hemorrhoidal Starch
NDC: 50730-1512 | Form: SUPPOSITORY
Manufacturer: H and P Industries, Inc. dba Triad Group
Category: otc | Type: HUMAN OTC DRUG LABEL
Date: 20091231

ACTIVE INGREDIENTS: STARCH, CORN 0.51 g/1 1
INACTIVE INGREDIENTS: BENZYL ALCOHOL; FAT, HARD; ALPHA-TOCOPHEROL ACETATE

DRUG FACTS

ACTIVE INGREDIENT

Topical starch, 51%

PURPOSE

Protectant

USE

- Provides temporary relief of the itching, burning and discomfort associated with hemorrhoids and other anorectal disorders
- Provides a coating to protect irritated tissue

WARNINGS

For rectal use only.

When using this product

do not exceed the recommended daily dosage unless directed by a doctor.

Stop use and ask a doctor

- in case of bleeding
- if condition worsens or does not improve within 7 days.

If pregnant or breast-feeding,

ask a health professional before use.

Keep out of reach of children

If swallowed, get medical help or contact a Poison Control Center right away.

DIRECTIONS

Adults:

- When practical, cleanse the affected area with mild soap and warm water. Rinse thoroughly.
- Gently dry by patting or blotting with toilet tissue or soft cloth before application of this product.
- Detach one suppository from strip of suppositories.
- Remove film before inserting into the rectum by holding the suppository upright. Carefully separate film by inserting tip of fingernail at film split.
- Carefully peel film slowly and evenly down both sides to expose suppository
- Avoid excessive handling of suppository, which is designed to melt at body temperature. If suppository seems soft, hold in film wrapper under cold water for 2 or 3 minutes.
- Insert one suppository rectally up to 6 times daily or after each bowel movement

Children under 12 years: ask a doctor.

OTHER INFORMATION

Store below 86° F (30° C).

INACTIVE INGREDIENTS

benzyl alcohol, hydrogenated vegetable oil, tocopheryl acetate

PACKAGE INFORMATION - REPRESENTATIVE LABEL

Compare to the active ingredient in TUCKS®*
HEMORRHOIDAL
SUPPOSITORIES
TOPICAL STARCH

- Relieves itching, burning and discomfort
- Protects and soothes irritated tissue

12 SUPPOSITORIES
*This product is not manufactured or distributed by Pfizer consumer Healthcare, Inc., owner of the registered trademark TUCKS®.